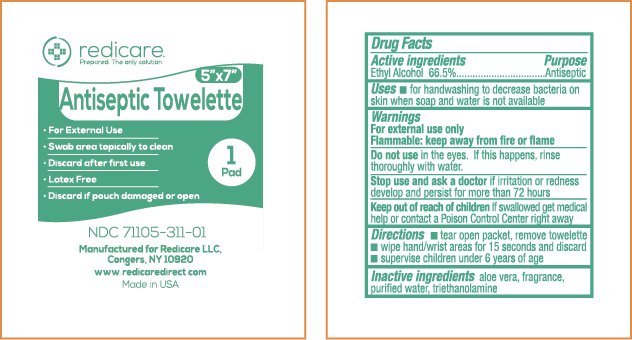 DRUG LABEL: REDICARE ANTISEPTIC WIPES
NDC: 71105-311 | Form: SWAB
Manufacturer: Redicare LLC
Category: otc | Type: HUMAN OTC DRUG LABEL
Date: 20191029

ACTIVE INGREDIENTS: ALCOHOL 665 mL/1 L
INACTIVE INGREDIENTS: WATER; TROLAMINE; ALOE

Antiseptic Wipes USA

Active Ingredient

Ethyl Alcohol 66.5%

Purpose

Antiseptic

Uses

- for handwashing to decrease bacteria on skin whenever soap and water are not readily available

WARNINGS

For external use only.

Flammable, keep away from fire or flame

Do not use

in the eyes. If this happens, rinse thoroughly with water.

Stop use and ask a doctor if

- irritation or redness develops and persists for more than 72 hours

Keep out of reach of children.

If swallowed, get medical help or contact a Poison Control Center right away.

DIRECTIONS

- Tear open packet, remove towelette
- wet hands and wrists thoroughly for 15 seconds and discard
- supervise children under 6 years of age

Inactive ingredients

Aloe vera, fragrance, purified water, triethanolamine